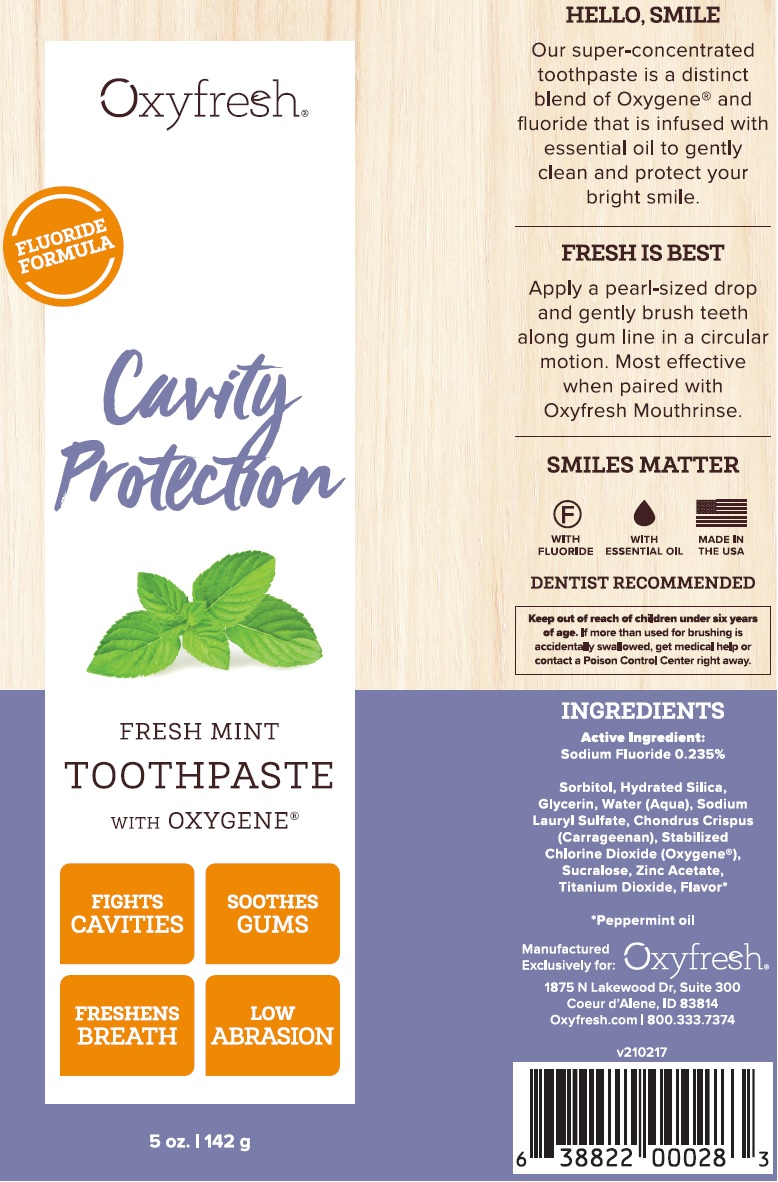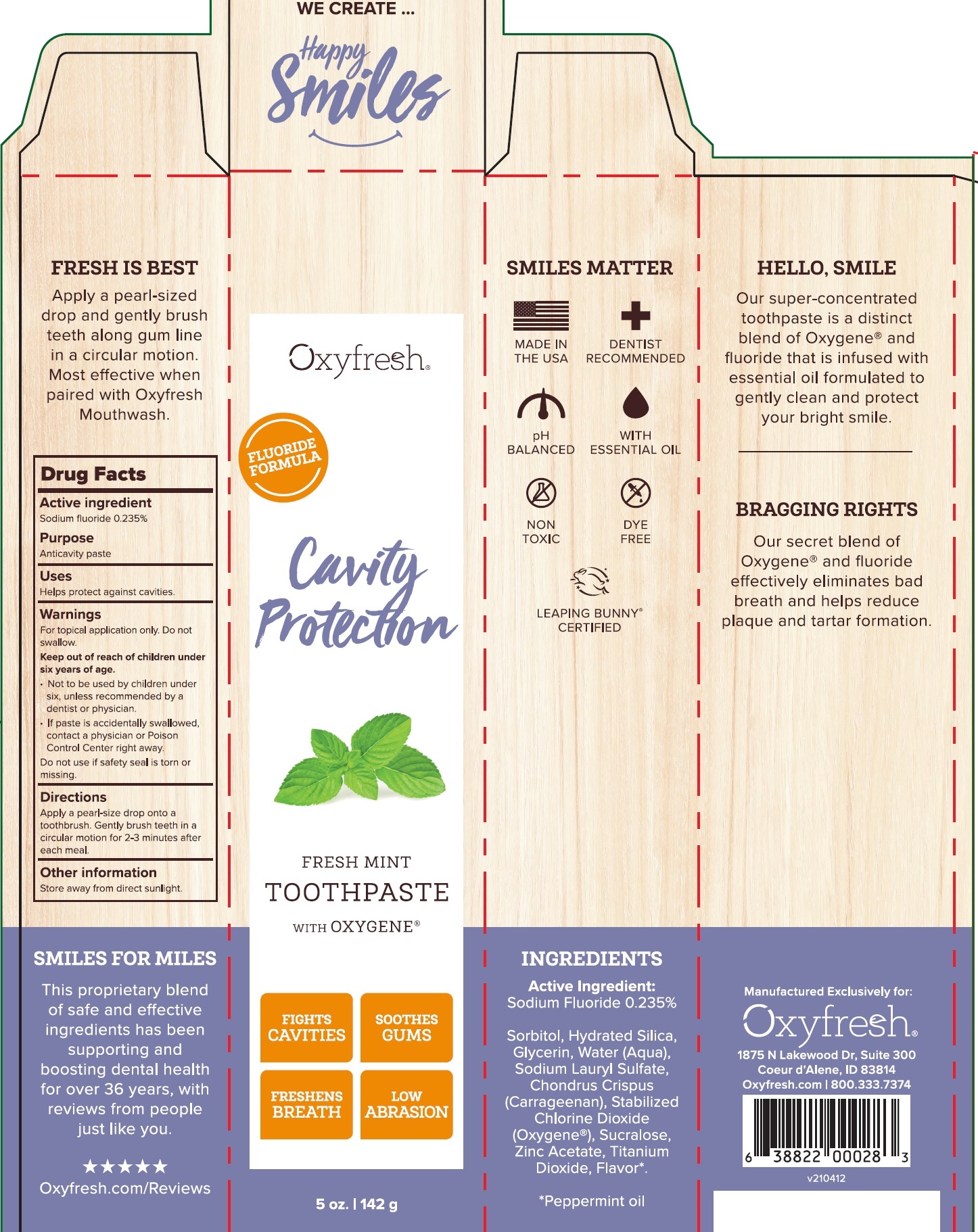 DRUG LABEL: Cavity Protection Fresh Mint
NDC: 63615-000 | Form: PASTE, DENTIFRICE
Manufacturer: Oxyfresh Worldwide Inc
Category: otc | Type: HUMAN OTC DRUG LABEL
Date: 20231025

ACTIVE INGREDIENTS: SODIUM FLUORIDE 2.35 mg/1 g
INACTIVE INGREDIENTS: SORBITOL; HYDRATED SILICA; GLYCERIN; WATER; SODIUM LAURYL SULFATE; CHONDRUS CRISPUS; OXYGEN; SUCRALOSE; ZINC ACETATE; TITANIUM DIOXIDE; PEPPERMINT OIL; CHLORINE DIOXIDE

Cavity Protection Fresh Mint Toothpaste

Active ingredient

Sodium fluoride 0.235%

Purpose

Anticavity paste

Uses

Helps protect against cavities.

Warnings

For topical application only. Do not swallow.

Keep out of reach of children

under six years of age.

- Not to be used by children under six, unless recommended by a dentist or physician.
- If paste is accidentally swallowed, contact a physician or Poison Control Center right away.

Do not use

if safety seal is torn or missing.

Directions

Apply a pearl-size drop onto a toothbrush. Gently brush teeth in a circular motion for 2-3 minutes after each meal.

Other information

Store away from direct sunlight.

INGREDIENTs

Sorbitol, Hydrated Silica, Glycerin, Water (Aqua), Sodium Lauryl Sulfate, Chondrus Crispus (Carrageenan), Stabilized Chlorine Dioxide (Oxygene), Sucralose, Zinc Acetate, Titanium Dioxide, Flavor*. Peppermint oil